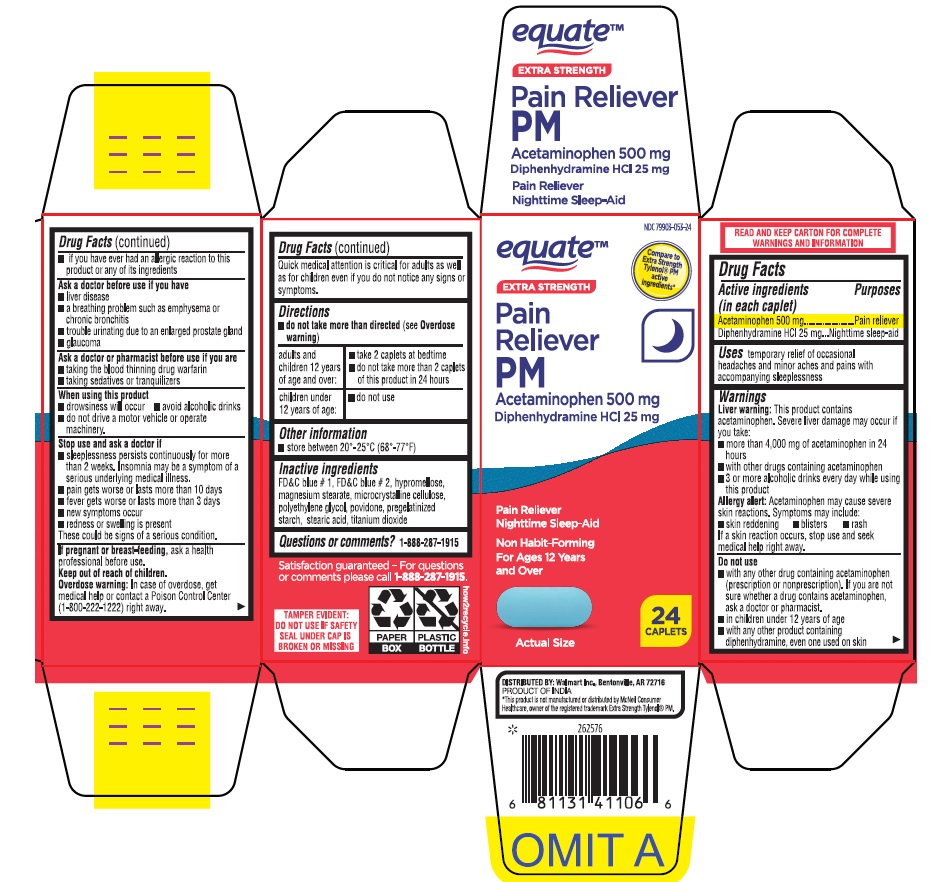 DRUG LABEL: EXTRA STRENGTH PAIN RELIEVER PM
NDC: 79903-053 | Form: TABLET
Manufacturer: WALMART INC.
Category: otc | Type: HUMAN OTC DRUG LABEL
Date: 20260127

ACTIVE INGREDIENTS: ACETAMINOPHEN 500 mg/1 1; DIPHENHYDRAMINE HYDROCHLORIDE 25 mg/1 1
INACTIVE INGREDIENTS: FD&C BLUE NO. 2; FD&C BLUE NO. 1; HYPROMELLOSE 2208 (15000 MPA.S); MAGNESIUM STEARATE; MICROCRYSTALLINE CELLULOSE; POLYETHYLENE GLYCOL 400; STARCH, CORN; POVIDONE K30; STEARIC ACID; TITANIUM DIOXIDE

EQUATE EXTRA STRENGTH PAIN RELIEVER PM (ACETAMINOPHEN PM)

Drug Facts

ACTIVE INGREDIENT

Active ingredients (in each caplet) | Purpose
Acetaminophen 500mg | Pain reliever
Diphenhydramine HCl 25mg | Nighttime Sleep aid

Uses

for the temporary relief of occasional headaches and minor aches and pains with accompanying sleeplessness

Warnings

Liver warning

This product contains acetaminophen. Severe liver damage may occur with this product if you take

- more than 4,000 mg of acetaminophen in 24 hours
- with other drugs containing acetaminophen
- 3 or more alcoholic drinks every day while you are using this product

Allergy alert

Acetaminophen may cause severe skin reactions. Symptoms may include:

- skin reddening
- blisters
- rash

If a skin reaction occurs, stop use and seek medical help right away.

Do not use

- with other products containing acetaminophen (prescription or nonprescription). If you are not sure whether a drug contains acetaminophen, ask a doctor or pharmacist
- in children under 12 years of age
- with any other products containing diphenhydramine, even one used on skin
- if you are allergic to acetaminophen or any of the inactive ingredients in this product

Ask a doctor before use if you have

- liver disease
- breathing problems such as emphysema or chronic bronchitis
- trouble urinating due to an enlargement of the prostate gland
- glaucoma

Ask a doctor or pharmacist before use if you are

- taking the blood thinning drug warfarin
- taking sedatives or tranquilizers

When using this product

- drowsiness will occur
- avoid alcoholic drinks
- do not drive a motor vehicle or operate machinery.

Stop use and ask a doctor if

- sleeplessness persists continuously for more than 2 weeks. Insomnia may be a symptom of a serious underlying medical illness
- pain gets worse or lasts for more than 10 days
- fever gets worse or lasts more than 3 days
- new symptoms occur
- redness or swelling is present

These could be signs of a serious condition.

PREGNANCY OR BREAST FEEDING

If pregnant or breast-feeding, ask a health professional before use.

Keep out of reach of children.

Overdose warning

Taking more than the directed dose (overdose) may cause liver damage. In case of overdose, get medical help or contact a Poison Control Center right away (1-800-222-1222).

Quick medical attention is critical for adults as well as for children even if you do not notice any signs or symptoms.

Directions

- do not take more than directed

(see Overdose warning)

adults and children 12 years of age and over: | - take 2 caplets at bedtime or as directed by a doctor - do not take more than 2 caplets in a 24 hour period
children under 12 years of age: | - do not use this adult product in children under 12 years of age. This will provide more than the recommended dose (overdose) and may cause liver damage

Other information

- each caplet contains: magnesium 0.05 mg
- store between 20°-25°C (68°-77°F)
- see end panel for lot number and expiration

Inactive ingredients

FD&C blue # 1, FD&C blue # 2, hypromellose, magnesium stearate, microcrystalline cellulose, polyethylene glycol-400, povidone, pregelatinized starch, stearic acid, titanium dioxide

Questions or comments?

1-888-287-1915

PRINCIPAL DISPLAY PANEL

EXTRA STRENGTH

PAIN RELIEVER PM

PAIN RELIEVER NIGHTTIME SLEEP AID

Acetaminophen 500 mg

Diphenhydramine HCl 25 mg